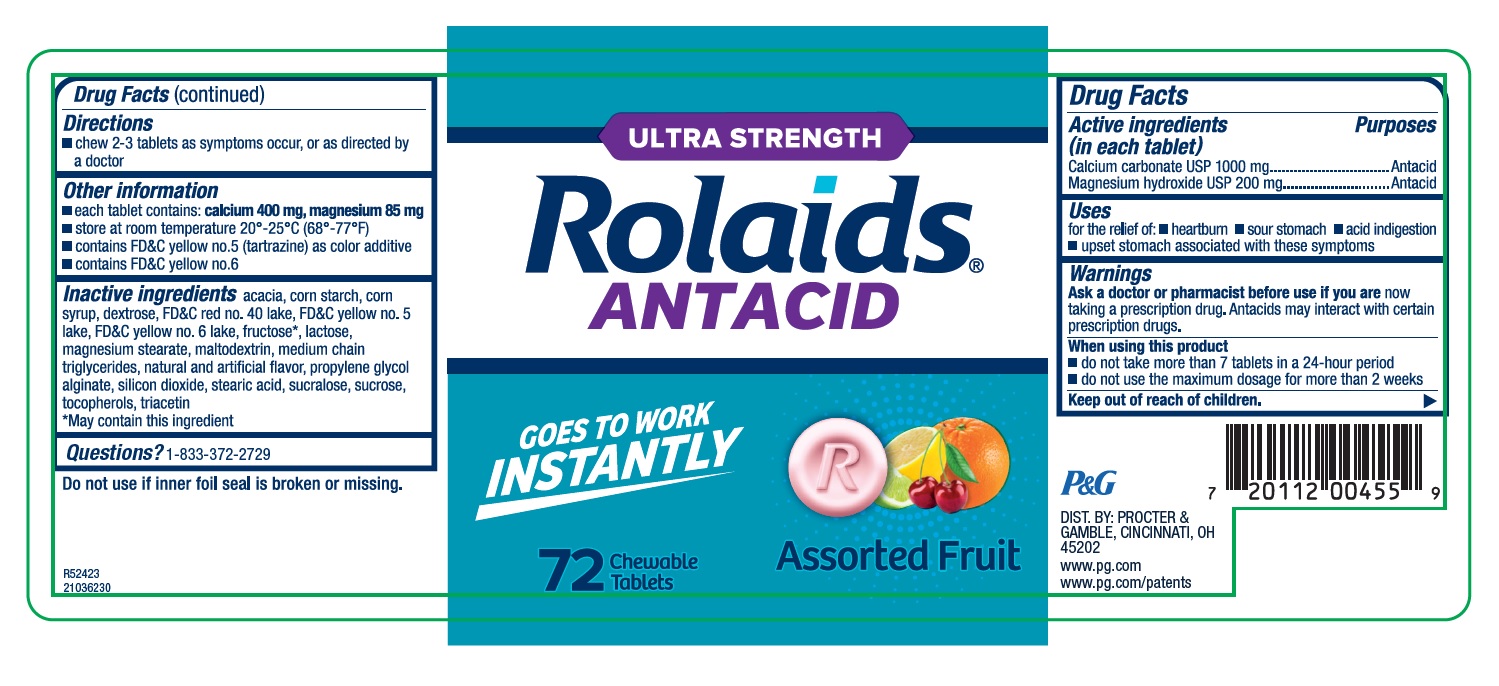 DRUG LABEL: Rolaids Ultra Strength Antacid
NDC: 69423-825 | Form: TABLET, CHEWABLE
Manufacturer: THE PROCTER & GAMBLE MANUFACTURING COMPANY
Category: otc | Type: HUMAN OTC DRUG LABEL
Date: 20251003

ACTIVE INGREDIENTS: CALCIUM CARBONATE 1000 mg/1 1; MAGNESIUM HYDROXIDE 200 mg/1 1
INACTIVE INGREDIENTS: DEXTROSE; MAGNESIUM STEARATE; FD&C RED NO. 40; SILICON DIOXIDE; STEARIC ACID; SUCRALOSE; SUCROSE; FD&C YELLOW NO. 5; FD&C YELLOW NO. 6; MALTODEXTRIN; ACACIA; STARCH, CORN; CORN SYRUP; FRUCTOSE; LACTOSE, UNSPECIFIED FORM; MEDIUM-CHAIN TRIGLYCERIDES; PROPYLENE GLYCOL ALGINATE; TOCOPHEROL; TRIACETIN; ALUMINUM OXIDE

Rolaids® Ultra Strength Antacid Chewable Tablets Assorted Fruit

Ultra Strength Rolaids Antacid, Assorted Fruit Chewable Tablets

Drug Facts

Active ingredient

(in each tablet)
Calcium carbonate USP 1000 mg
Magnesium hydroxide USP 200 mg

Purpose

Antacid

Antacid

Uses

for the relief of:

- heartburn
- sour stomach
- acid indigestion
- upset stomach associated with these symptoms

Warnings

Ask a doctor or pharmacist before use if you are

now taking a prescription drug. Antacids may interact with certain prescription drugs.

When using this product

- do not take more than 7 tablets in a 24-hour period
- do not use the maximum dosage for more than 2 weeks

Directions

- chew 2-3 tablets as symptoms occur, or as directed by a doctor

Other information

each tablet contains: calcium 400 mg, magnesium 85 mg

- store at room temperature 20°-25°C (68°-77°F)
- contains FD&C yellow no.5 (tartrazine) as color additive
- contains FD & C yellow no.6

Inactive ingredients

acacia, corn starch, corn syrup, dextrose, FD&C red no. 40 lake, FD&C yellow no. 5 lake, FD&C yellow no. 6 lake, fructose*, lactose, magnesium stearate, maltodextrin, medium chain triglycerides, natural and artificial flavor, propylene glycol alginate, silicon dioxide, stearic acid, sucralose, sucrose, tocopherols, triacetin

*May contain this ingredient

Questions?

1-833-372-2729

Tamper Evident

Do not use if inner foil seal is broken or missing.

DIST. BY: PROCTER & GAMBLE, CINCINNATI, OH 45202

PRINCIPAL DISPLAY PANEL

ULTRA STRENGTH
Rolaids®ANTACID

GOES TO WORK INSTANTLY
Assorted Fruit
72 Chewable Tablets